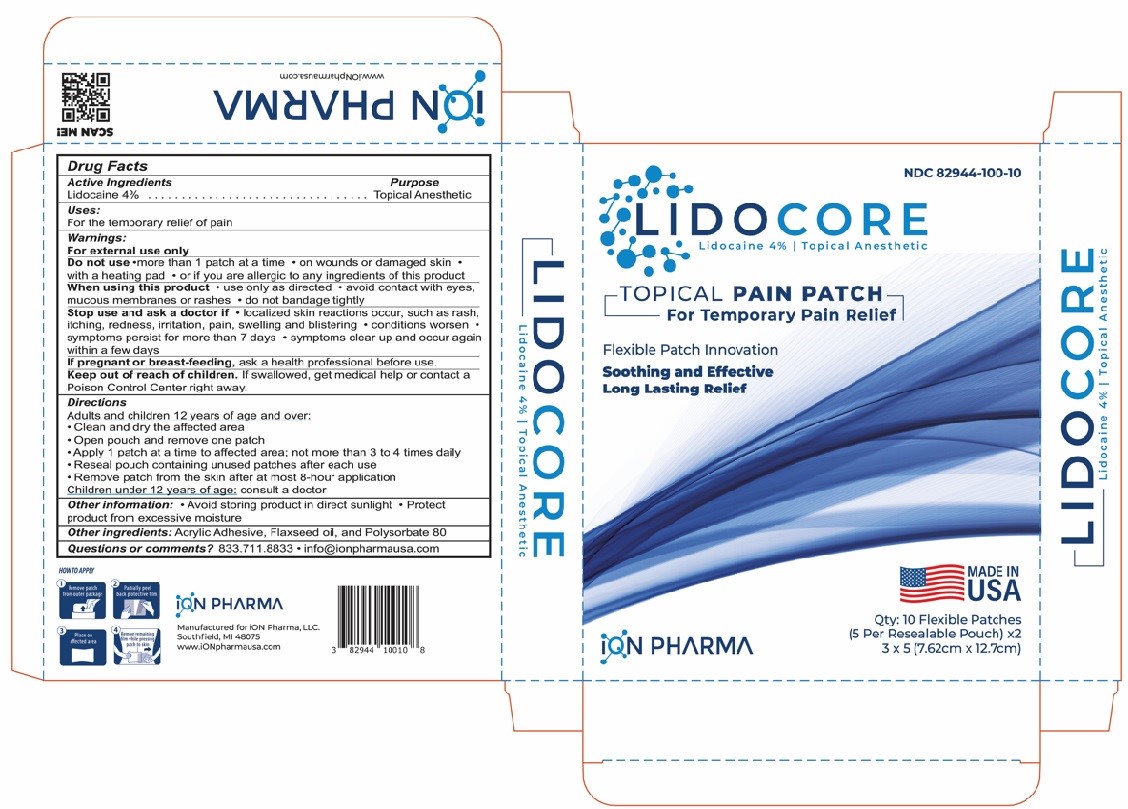 DRUG LABEL: LIDOCORE
NDC: 82944-100 | Form: PATCH
Manufacturer: Ion Pharma, LLC
Category: otc | Type: HUMAN OTC DRUG LABEL
Date: 20260114

ACTIVE INGREDIENTS: LIDOCAINE 4 g/1 1
INACTIVE INGREDIENTS: ACRYLIC ACID; LINSEED OIL; POLYSORBATE 80

LIDOCORE
Lidocaine 4% Topical Anesthetic
TOPICAL PAIN PATCH
For Temporary Pain Relief

Drug Facts

Active Ingredients
Lidocaine 4%
Purpose
Topical Anesthetic
Uses:
For the temporary relief of pain
Warnings:
For external use only
DO NOT USE
Do not use - more than 1 patch at a time - on wounds or damaged skin - with a heating pad - or if you are allergic to any ingredients of this product
WHEN USING
When using this product - use only as directed - avoid contact with eyes, mucous membranes or rashes - do not bandage tightly
STOP USE
Stop use and ask a doctor if - localized skin reactions occur, such as rash, itching, redness, irritation, pain, swelling and blistering - conditions worsen - symptoms persist for more than 7 ...
PREGNANCY OR BREAST FEEDING
If pregnant or breast-feeding, ask a health professional before use.
KEEP OUT OF REACH OF CHILDREN
Keep out of reach of children. If swallowed, get medical help or contact a Poison Control Center right away.

Active Ingredients

Lidocaine 4%

Purpose

Topical Anesthetic

Uses:

For the temporary relief of pain

Warnings:

For external use only

Do not use

- more than 1 patch at a time
- on wounds or damaged skin
- with a heating pad
- or if you are allergic to any ingredients of this product

When using this product

- use only as directed
- avoid contact with eyes, mucous membranes or rashes
- do not bandage tightly

Stop use and ask a doctor if

- localized skin reactions occur, such as rash, itching, redness, irritation, pain, swelling and blistering
- conditions worsen
- symptoms persist for more than 7 days
- symptoms clear up and occur again within a few days

Pregnancy or breast feeding section

If pregnant or breast-feeding,ask a health professional before use.

Keep out of reach of children.If swallowed, get medical help or contact a Poison Control Center right away.

Directions

Adults and children 12 years of age and over:

- Clean and dry the affected area
- Open pouch and remove one patch
- Apply 1 patch at a time to affected area; not more than 3 to 4 times daily
- Reseal pouch containing unused patches after each use
- Remove patch from the skin after at most 8-hour application

Children under 12 years of age:consult a doctor

Other information:

- Avoid storing product in direct sunlight
- Protect product from excessive moisture

INACTIVE INGREDIENT

Other ingredients:Acrylic Adhesive, Flaxseed oil, and Polysorbate 80

Question Section

Questions or comments?833.711.8833

- info@ionpharmausa.com

PRINCIPAL DISPLAY PANEL

NDC 82944-100-10

LIDOCORE
Lidocaine 4% Topical Anesthetic

TOPICAL PAIN PATCH
For Temporary Pain Relief

Flexible Patch Innovation

Soothing and Effective
Long Lasting Relief

MADE IN USA

Qty: 10 Flexible Patches

(5 per Resealable Pouch) x2

3 x 5 (7.62cm x 12.7cm)

ION PHARMA